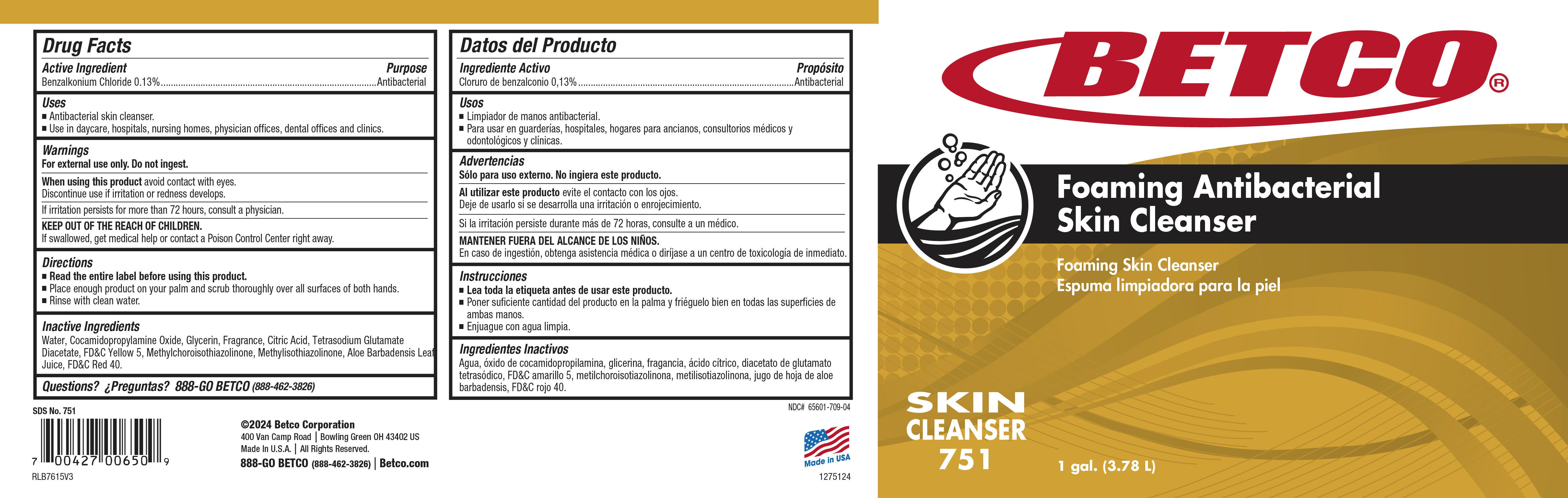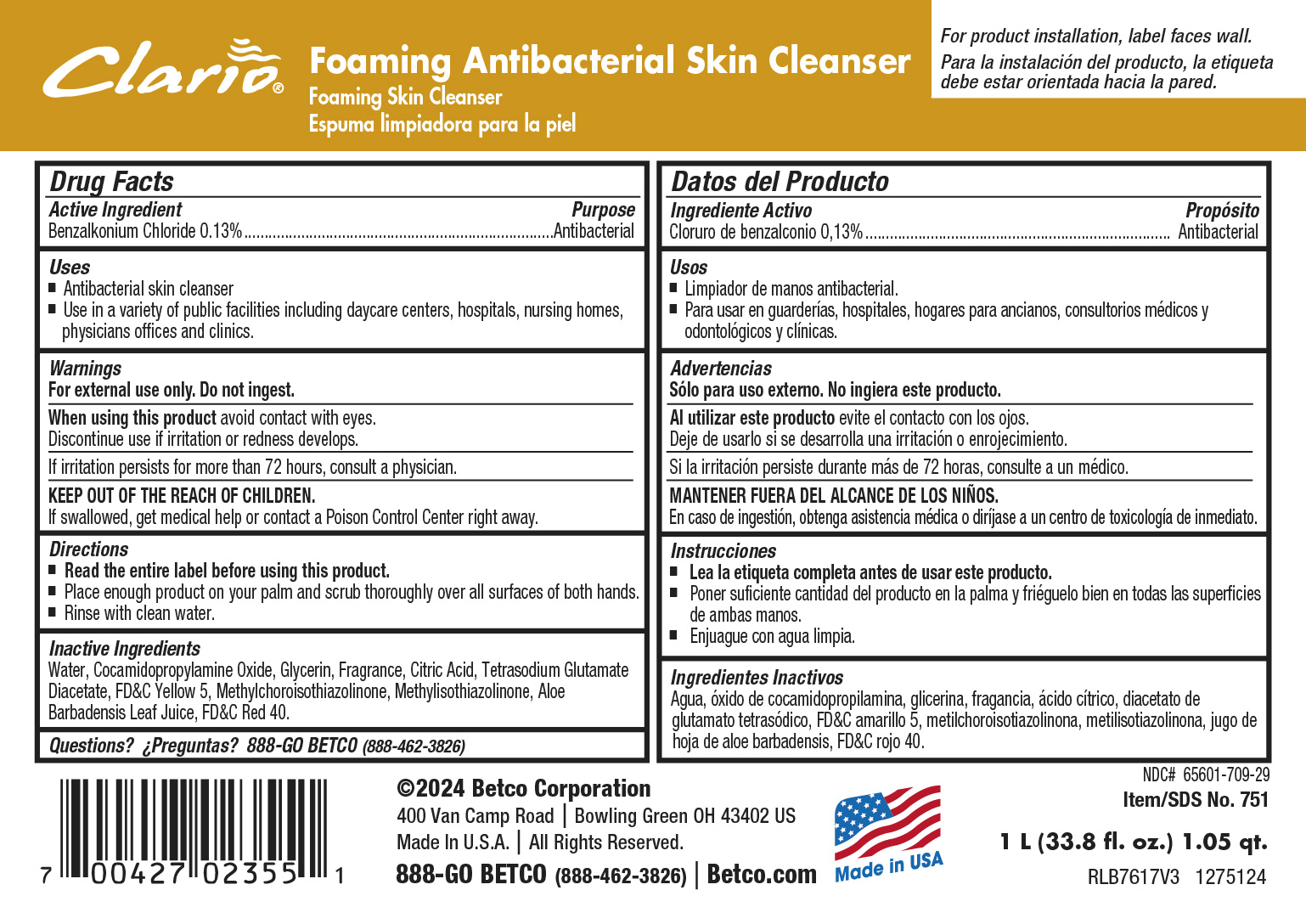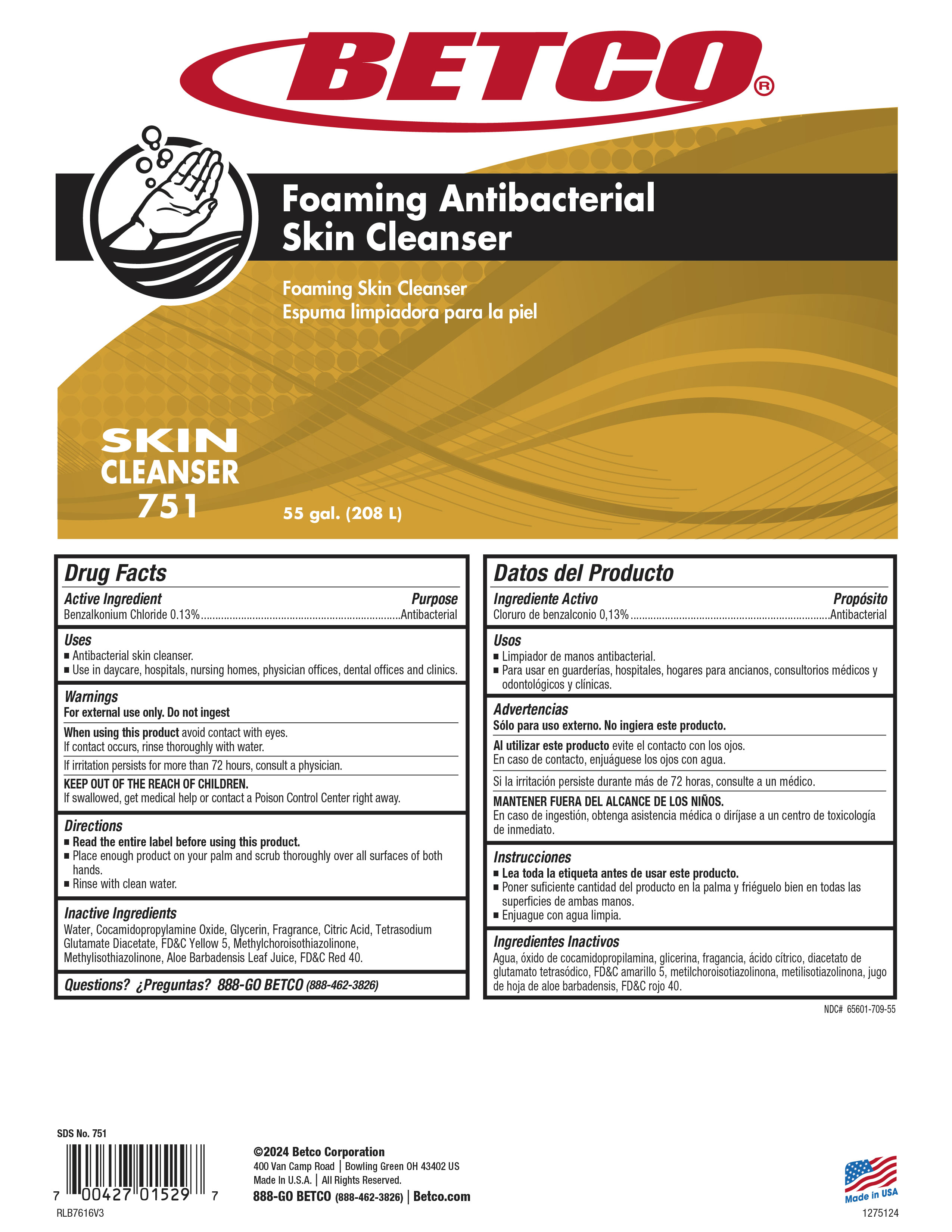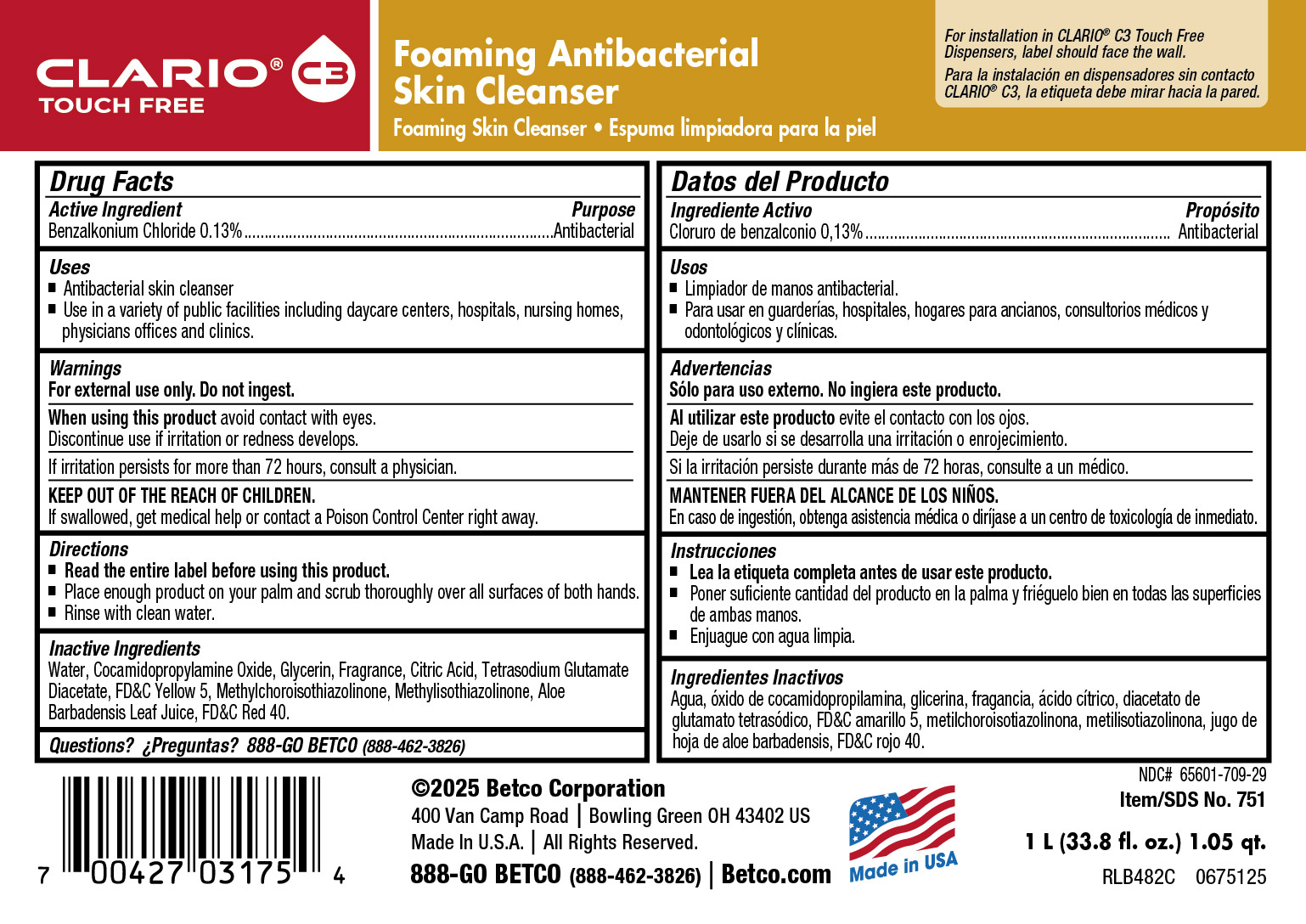 DRUG LABEL: Antibacterial Foaming Skin Cleanser
NDC: 65601-709 | Form: SOAP
Manufacturer: Betco Corporation, Ltd.
Category: otc | Type: HUMAN OTC DRUG LABEL
Date: 20260226

ACTIVE INGREDIENTS: BENZALKONIUM CHLORIDE 0.13 mg/1 mL
INACTIVE INGREDIENTS: FD&C YELLOW NO. 5; GERANIOL; 2-TERT-BUTYLCYCLOHEXYLOXYBUTANOL; DIHYDROMYRCENOL; TETRASODIUM GLUTAMATE DIACETATE; ANHYDROUS CITRIC ACID; ALLYL HEPTANOATE; WATER; GLYCERIN; MAGNESIUM NITRATE; ALCOHOL; ALOE VERA LEAF; METHYLCHLOROISOTHIAZOLINONE; METHYLISOTHIAZOLINONE; FD&C RED NO. 40; COCAMIDOPROPYLAMINE OXIDE; LINALOOL, (+/-)-; 2-TERT-BUTYLCYCLOHEXYL ACETATE; CITRAL; N-ALKYL DIMETHYL BENZYL AMMONIUM CHLORIDE (C12-C18); HYDROGEN PEROXIDE; LIMONENE, (+)-

Antibacterial Foaming Skin Cleanser

Active Ingredient

Benzalkonium Chloride 0.13%

Uses

- Antibacterial skin cleanser.
- Use in a variety of public facilities including daycare centers, hospitals, nursing homes, physicians offices.

Warnings

- For external use only.
- Avoid contact with eyes.
- If contact occurs, rinse thoroughly with water.
- Discontinue use is irritation or redness develops.
- If irritation persists for more than 72 hours, consult a physician.
- KEEP OUT OF REACH OF CHILDREN.
- If swallowed, get medical help or contact a Poison Control Center right away.

Directions

- Read the entire label before using this product.
- Dispense 2 pumps of product onto palm of hand and scrub thoroughly over all surfaces of both hands.
- Rinse with clean water.

Inactive Ingredients

Water, Potasium Cocoate, Propylene Glycol, Glycerin, Tetrasodium EDTA, Fragrance, Bronopol, Sodium Citrate, Magnesium Nitrate, Sodium Hydroxyacetate, Ethanol, Aloe Barbadensis Leaf Juice, Trisodium Nitriloacetate, FD&C Yellow #5, Sodium Hydroxide, Methylchloroisothiazolinone, Magnesium Chloride, Methylisothiazolinone, FD&C Red #40.

Purpose

Antibacterial

KEEP OUT OF REACH OF CHILDREN